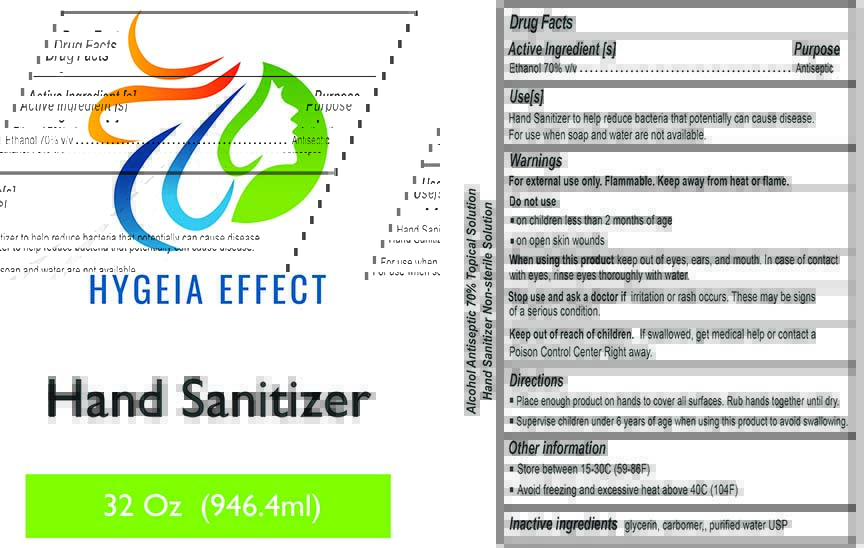 DRUG LABEL: Hygeia Effect Hand Sanitizer
NDC: 76605-119 | Form: GEL
Manufacturer: Pecan Bayou Enterprises, LLC
Category: otc | Type: HUMAN OTC DRUG LABEL
Date: 20210303

ACTIVE INGREDIENTS: ALCOHOL 662 mL/946 mL
INACTIVE INGREDIENTS: CARBOMER 940 1 mL/946 mL; GLYCERIN 84 mL/946 mL; WATER 199 mL/946 mL

Purpose

Antiseptic, Hand Sanitizer

Use

Hand Sanitizer to help reduce bacteria that can potentially cause disease. For use when soap and water are not available.

Active Ingredient(s)

Alcohol 80% v/v. Purpose: Antiseptic

Warnings

For external use only. Flammable. Keep away from heat or flame.

DO NOT USE

-In children less than 2 months of age
-On open skin wounds

When using this product keep out of the eyes, ears and mouth. In case of contact with eyes, rinse thoroughly with water.

Stop use and ask a doctor if rash or irritation occurs. These may be signs of a serious condition.

Keep out of the reach of children. If swallowed get medical help or contact a Poison Control Center right away.

Stop use and ask a doctor is rash or irritation occurs. This may be a sign of a serious condition.

KEEP OUT OF REACH OF CHILDREN

Keep out of the reach of children. If swallowed get medical help or contact a Poison Control Center right away.

DOSAGE AND ADMINISTRATION

Place enough on hands to cover all surfaces. Rub hands until dry.
Supervise children under 6 years of age when using this product to avoid swallowing.

Other Information

Store between 15-50C (59-86F)

Avoid freezing and excessive heat above 40C (104F)

Inactive Ingredients

Water, Glycerine USP, Carbomer, TEA